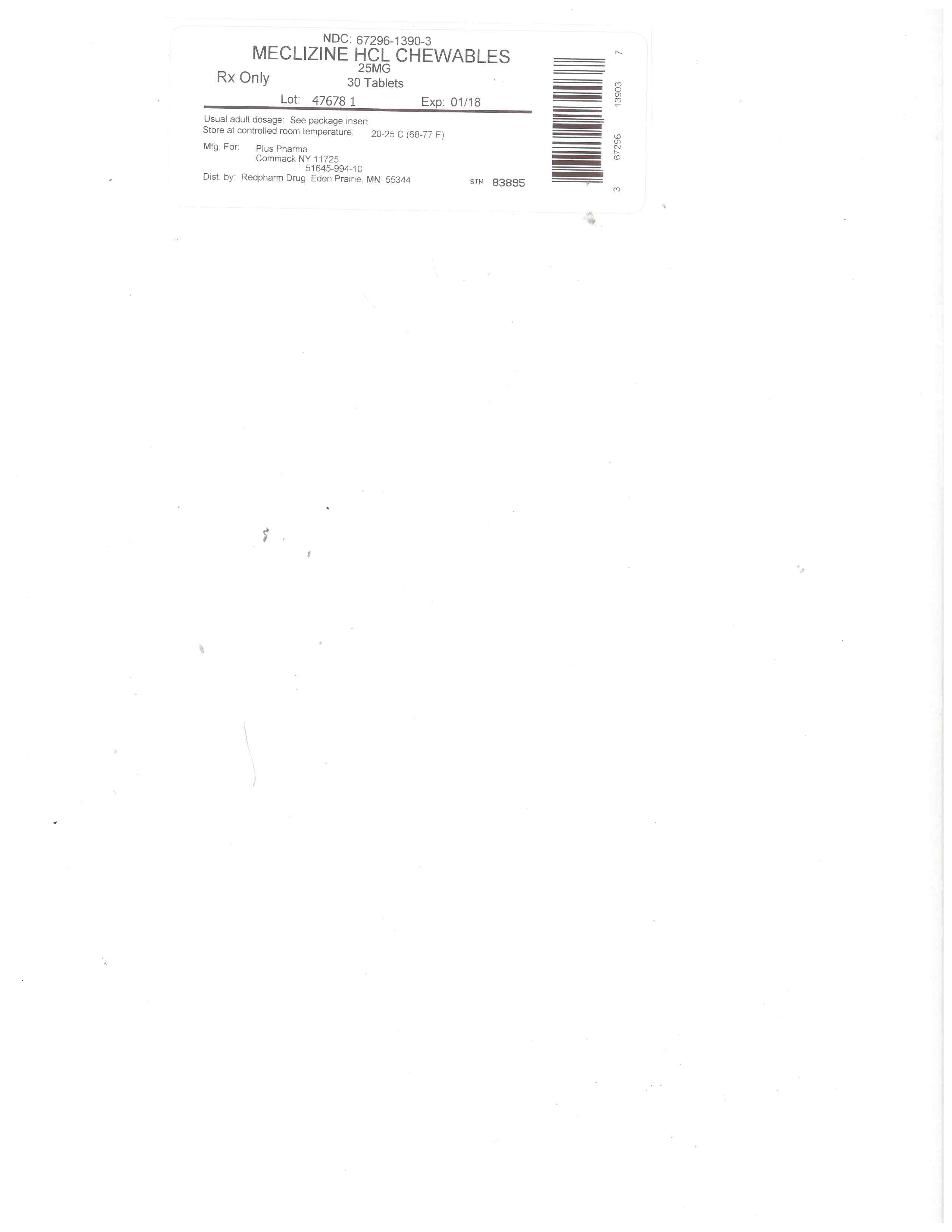 DRUG LABEL: Meclizine HCl 25 mg
NDC: 67296-1390 | Form: TABLET, CHEWABLE
Manufacturer: RedPharm Drug, Inc.
Category: otc | Type: HUMAN OTC DRUG LABEL
Date: 20200120

ACTIVE INGREDIENTS: MECLIZINE HYDROCHLORIDE 25 mg/1 1
INACTIVE INGREDIENTS: CROSCARMELLOSE SODIUM; FD&C RED NO. 40; CELLULOSE, MICROCRYSTALLINE; TRICALCIUM PHOSPHATE; ASPARTAME; SUCROSE; DEXTROSE; MAGNESIUM STEARATE; MALTODEXTRIN; SILICON DIOXIDE; SODIUM SULFATE

ACTIVE INGREDIENT (IN EACH CHEWABLE TABLET)

Meclizine HCl, USP 25 mg

PURPOSE

Antiemetic

USES

prevents and treats nausea, vomiting or dizziness due to motion sickness

WARNINGS

Do not use in children under 12 years of age unless directed by a doctor.

ASK DOCTOR

Ask a doctor before use if you have

glaucoma
a breathing problem such as emphysema or chronic bronchitis
trouble urinating due to an enlarged prostate gland

ASK DOCTOR/PHARMACIST

Ask a doctor or pharmacist before use if you are taking sedatives or tranquilizers.

PREGNANCY OR BREAST FEEDING

If pregnant or breast-feeding, ask a health professional before use

KEEP OUT OF REACH OF CHILDREN

In case of overdose, get medical help or contact the poison control center immediately.

DIRECTIONS

Dosage should be taken one hour before travel starts.
Adults and children 12 years of age and older: Chew 1-2 tablets once daily or as directed by a doctor
Children under 12 years: do not give this product to children under 12 years of age unless directed by a doctor.

OTHER INFORMATION

store at room temperature

OTHER SAFETY INFORMATION

Phenylketonurics: Contains phenylalanine 0.28 mg per tablet
Do not use if imprinted safety seal under cap is broken or missing

INACTIVE INGREDIENTS

aspartame, croscarmellose sodium, dextrose, FD&C Red #40 Lake, magnesium stearate, maltodextrin, microcrystalline cellulose, natural and artificial flavors, silicon dioxide, sodium sulfate, sugar, tricalcium phosphate.

QUESTIONS OR COMMENTS?

If you have any questions or comments or to report an adverse event, please contact (800) 795-9775.

WHEN USING

When using this product

may cause drowsiness
alcohol, sedatives, and tranquilizers may increase drowsiness
avoid alcoholic drinks
use caution when driving a motor vehicle or operating machinery

PURPOSE

Antiemetic